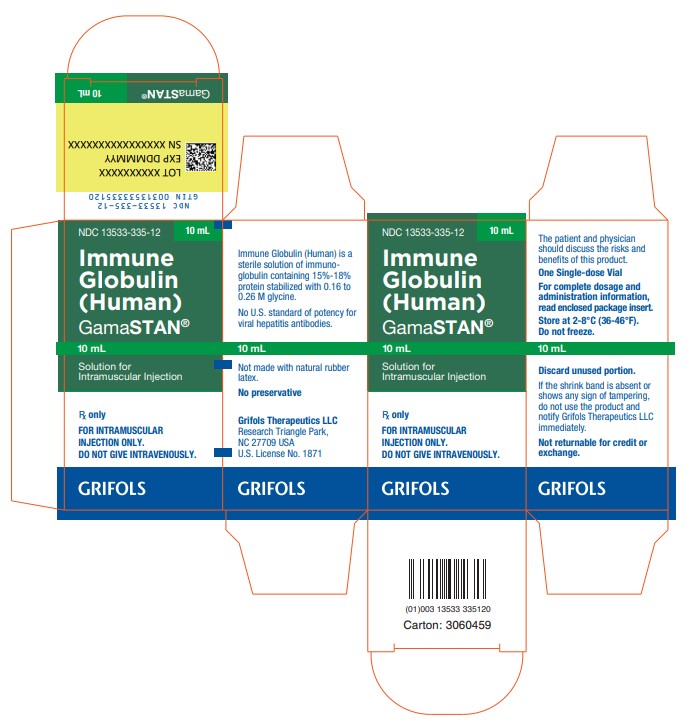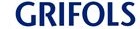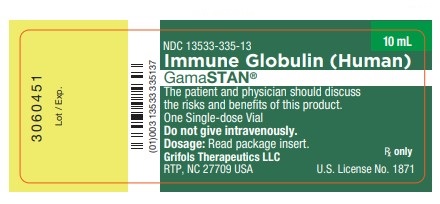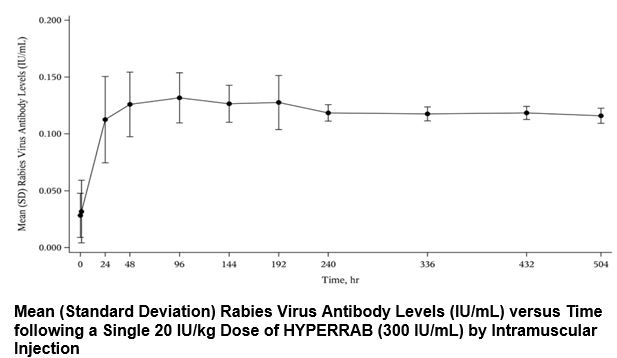 DRUG LABEL: GamaSTAN
NDC: 13533-335 | Form: INJECTION, SOLUTION
Manufacturer: GRIFOLS USA, LLC
Category: other | Type: PLASMA DERIVATIVE
Date: 20240920

ACTIVE INGREDIENTS: Human Immunoglobulin G 0.165 g/1 mL
INACTIVE INGREDIENTS: Glycine; Water

HIGHLIGHTS OF PRESCRIBING INFORMATION

These highlights do not include all the information needed to use GAMASTAN safely and effectively. See full prescribing information for GAMASTAN.
GAMASTAN[immune globulin (human)], solution for intramuscular injection
Initial U.S. Approval: 1944

WARNING: THROMBOSIS

See full prescribing information for complete boxed warning

- Thrombosis may occur with immune globulin products, including GAMASTAN. Risk factors may include: advanced age, prolonged immobilization, hypercoagulable conditions, history of venous or arterial thrombosis, use of estrogens, indwelling central vascular catheters, hyperviscosity, and cardiovascular risk factors. Thrombosis may occur in the absence of known risk factors. [see Warnings and Precautions (5.2), Patient Counseling Information (17)]
- For patients at risk of thrombosis, do not exceed the recommended dose of
  GAMASTAN. Ensure adequate hydration in patients before administration. Monitor for signs and symptoms of thrombosis and assess blood viscosity in patients at risk for hyperviscosity. [Warnings and Precautions (5.2)]

1 INDICATIONS AND USAGE

GAMASTAN is a human immune globulin indicated:

- For prophylaxis following exposure to hepatitis A. (1.1)
- To prevent or modify measles in a susceptible person exposed fewer than 6 days previously. (1.2)
- To modify varicella. (1.3)
- To modify rubella in exposed women who will not consider a therapeutic abortion. (1.4)
- Not indicated for routine prophylaxis or treatment of viral hepatitis type B, rubella, poliomyelitis, mumps or varicella. (1.5)

2 DOSAGE AND ADMINISTRATION

For intramuscular use only. Do not administer intravenously.

Indication | Dosage | Instruction
Hepatitis A (2.1) | 0.1 mL/kg | Administer within two weeks of prior exposure to hepatitis A.
Hepatitis A (2.1) |  | Administer before departure to persons traveling to areas with endemic hepatitis A:
Hepatitis A (2.1) | 0.1 mL/kg | if the length of stay will be up to 1 month
Hepatitis A (2.1) | 0.2 mL/kg | if the length of stay will be up to 2 months; repeat every 2 months for longer stays.
Measles (2.1) | 0.25 mL/kg | Administer within 6 days of exposure.
Measles (2.1) | 0.5 mL/kg | Immediately administer (maximum dose, 15 mL) to an immunocompromised child.
Varicella (2.1) | 0.6 mL/kg to 1.2 mL/kg | Administer promptly if Varicella-Zoster Immune Globulin (Human) is unavailable.
Rubella (2.1) | 0.55 mL/kg | Only administer to exposed pregnant women who will not consider a therapeutic abortion.

3 DOSAGE FORMS AND STRENGTHS

GAMASTAN is a sterile, 16.5% protein solution supplied in 2 mL and 10 mL single-dose vials. (3)

4 CONTRAINDICATIONS

- Anaphylactic or severe systemic hypersensitivity reactions to Immune Globulin (Human) (4)
- IgA deficient patients with antibodies against IgA and a history of hypersensitivity (4)

5 WARNINGS AND PRECAUTIONS

- Patients with known hypersensitivity to immune globulin preparations are at greater risk of developing severe hypersensitivity and anaphylactic reactions. Have epinephrine available immediately to treat any acute severe hypersensitivity reactions. (5.1)
- Do not administer intravenously because of the potential for serious reactions (e.g., Renal Dysfunction/Failure/Hemolysis, Transfusion-Related Acute Lung Injury [TRALI]). (5.3)
- GAMASTAN is made from human blood; it may carry a risk of transmitting infectious agents, e. g, viruses, the variant Creutzfeldt-Jakob disease (vCJD) agent and, theoretically, the Creutzfeldt-Jakob disease (CJD) agent. (5.4)

6 ADVERSE REACTIONS

The most common adverse reaction reported for GAMASTAN S/D during post-approval use was fatigue. (6)

To report SUSPECTED ADVERSE REACTIONS, contact Grifols Therapeutics LLC at 1-800-520-2807 or FDA at 1-800-FDA-1088 or www.fda.gov/medwatch.

7 DRUG INTERACTIONS

- Defer live vaccine administration for up to 6 months. (7)

FULL PRESCRIBING INFORMATION

WARNING: THROMBOSIS

- Thrombosis may occur with immune globulin products, including GAMASTAN. Risk factors may include: advanced age, prolonged immobilization, hypercoagulable conditions, history of venous or arterial thrombosis, use of estrogens, indwelling central vascular catheters, hyperviscosity, and cardiovascular risk factors. Thrombosis may occur in the absence of known risk factors. [see Warnings and Precautions (5.2), Patient Counseling Information (17)]
- For patients at risk of thrombosis, do not exceed the recommended dose of GAMASTAN. Ensure adequate hydration in patients before administration. Monitor for signs and symptoms of thrombosis and assess blood viscosity in patients at risk for hyperviscosity. [Warnings and Precautions (5.2)]

1 INDICATIONS AND USAGE

GAMASTAN is a human immune globulin indicated for:

1.1 Hepatitis A

GAMASTAN is indicated for prophylaxis following exposure to hepatitis A.(1,2) The prophylactic value of GAMASTAN is greatest when given before or soon after exposure to hepatitis A. GAMASTAN is not indicated in persons with clinical manifestations of hepatitis A or in those exposed more than 2 weeks previously.

1.2 Measles (Rubeola)

GAMASTAN is indicated to prevent or modify measles in a susceptible person exposed fewer than 6 days previously.(3) A susceptible person is one who has not been vaccinated and has not had measles previously.

- GAMASTAN may be especially indicated for susceptible household contacts of measles patients, particularly contacts under 1 year of age, for whom the risk of complications is highest.(3)
- GAMASTAN is also indicated for pregnant women without evidence of immunity.
- Do not give GAMASTAN and measles vaccine at the same time. If a child is older than 12 months and has received GAMASTAN, give measles vaccine about five months later when the measles antibody titer will have disappeared.(3,4) [see Drug Interactions (7)] If a susceptible child exposed to measles is immunocompromised, give GAMASTAN immediately.

1.3 Varicella

GAMASTAN is indicated to modify varicella.

- Passive immunization against varicella in immunosuppressed patients is best accomplished by use of Varicella Zoster Immune Globulin (Human). If unavailable, GAMASTAN, promptly given, may also modify varicella. (5,6)

1.4 Rubella

GAMASTAN is indicated to modify rubella in exposed women who will not consider a therapeutic abortion.

- Some studies suggest that the use of GAMASTAN in exposed, susceptible women can lessen the likelihood of infection and fetal damage; therefore, GAMASTAN may benefit those women who will not consider a therapeutic abortion.(7)
- Do not give GAMASTAN for routine prophylaxis of rubella in early pregnancy to an unexposed woman.(7)

1.5 Limitations of Use

- GAMASTAN is not standardized with respect to antibody titers against hepatitis B surface antigen (HBsAg) and must not be used for prophylaxis of viral hepatitis type B. Prophylactic treatment to prevent hepatitis B can best be accomplished with use of Hepatitis B Immune Globulin (Human), often in combination with Hepatitis B Vaccine.(8)
- GAMASTAN is not indicated for routine prophylaxis or treatment of rubella, poliomyelitis, mumps, or varicella.

2 DOSAGE AND ADMINISTRATION

For intramuscular use only.

Do not administer intravenously.

2.1 Dose

Indication | Dosage | Instruction
Prophylaxis for exposure to hepatitis A | 0.1 mL/kg [0.05 milliliter per pound] | Administer within two weeks of prior exposure for household and institutional hepatitis A case contacts.
Prophylaxis for exposure to hepatitis A |  | Administer before departure to persons traveling to areas with endemic hepatitis A:
Prophylaxis for exposure to hepatitis A | 0.1 mL/kg | if the length of stay will be up to 1 month(9,10)
Prophylaxis for exposure to hepatitis A | 0.2 mL/kg | if the length of stay will be up to 2 months(9,10)
Prophylaxis for exposure to hepatitis A | 0.2 mL/kg | if the length of stay will be 2 months or longer; repeat every 2 months.(9,10)
Prevent or modify measles in a susceptible person exposed fewer than six days previously | 0.25 mL/kg [0.11 milliliter per pound] | Administer to a susceptible person within 6 days of exposure.
Prevent or modify measles in a susceptible person exposed fewer than six days previously | 0.5 mL/kg | Immediately administer (maximum dose, 15 mL) to an immunocompromised child.
Modify varicella | 0.6 mL/ kg to 1.2 mL/kg | Administer promptly only if Varicella-Zoster Immune Globulin (Human) is unavailable.
Modify rubella only in an exposed woman who will not consider a therapeutic abortion | 0.55 mL/kg | Only administer to an exposed pregnant woman who will not consider a therapeutic abortion.

2.2 Preparation and Handling

- If the product shows any sign of tampering, do not use it and notify Grifols Therapeutics LLC immediately [1-800-520-2807].
- Visually inspect parenteral drug products for particulate matter and discoloration prior to administration, whenever solution and container permit. GAMASTAN is a clear or slightly opalescent, and colorless to pale yellow sterile solution.

2.3 Administration

- Administer GAMASTAN intramuscularly, preferably in the anterolateral aspects of the upper thigh and the deltoid muscle of the upper arm. Do not use the gluteal region as an injection site because of the risk of injury to the sciatic nerve.(4) [see Warnings and Precautions (5.3)]
- Draw back on the plunger of the syringe before injection in order to be certain that the needle is not in a blood vessel. [see Warnings and Precautions (5.3)]
- Divide and inject doses greater than 10 mL into several muscle sites to reduce local pain and discomfort. An individual decision as to which muscle is injected must be made for each patient based on the volume of material to be administered.
- If Hepatitis A Vaccine is recommended along with GAMASTAN, administer simultaneously but at separate anatomical sites.

3 DOSAGE FORMS AND STRENGTHS

GAMASTAN is a sterile, 16.5% protein solution supplied in 2 mL and 10 mL single-dose vials.

4 CONTRAINDICATIONS

GAMASTAN is contraindicated in:

- Anaphylactic or severe systemic hypersensitivity reactions to Immune Globulin (Human).(11) [see Warnings and Precautions (5.1)]
- IgA deficient patients with antibodies against IgA and a history of hypersensitivity.(11)

5 WARNINGS AND PRECAUTIONS

5.1 Hypersensitivity Reactions

Administer GAMASTAN cautiously to patients with a history of prior systemic allergic reactions following the administration of human immunoglobulin preparations.(11) Have epinephrine available for treatment of acute allergic symptoms, should they occur.

Do not perform skin tests. In most patients the intradermal injection of concentrated gamma globulin solution with its buffers causes a localized area of inflammation which can be misinterpreted as a positive allergic reaction. In actuality, this does not represent an allergy; rather, it is localized tissue irritation of a chemical nature. Misinterpretation of the results of such tests can lead the physician to withhold beneficial human immunoglobulin from a patient who is not actually allergic to this material.

5.2 Thrombosis

Thrombosis may occur following treatment with immune globulin products, including GAMASTAN.(12-14) Risk factors may include: advanced age, prolonged immobilization, hypercoagulable conditions, history of venous or arterial thrombosis, use of estrogens, indwelling central vascular catheters, hyperviscosity, and cardiovascular risk factors. Thrombosis may occur in the absence of known risk factors.

Consider baseline assessment of blood viscosity in patients at risk for hyperviscosity, including those with cryoglobulins, fasting chylomicronemia/markedly high triacylglycerols (triglycerides), or monoclonal gammopathies. For patients at risk of thrombosis, do not exceed the recommended dose of GAMASTAN. Ensure adequate hydration in patients before administration. Monitor for signs and symptoms of thrombosis and assess blood viscosity in patients at risk for hyperviscosity. [see Boxed Warning, Patient Counseling Information (17)]

5.3 Systemic Reactions

Inject intramuscularly only. Do not administer GAMASTAN intravenously because of the potential for serious reactions (e.g., Renal Dysfunction/Failure/Hemolysis, Transfusion-Related Acute Lung Injury [TRALI]). Do not inject into a blood vessel. [see Dosage and Administration (2.3)]

5.4 Transmissible Infectious Agents

GAMASTAN is made from human blood and may carry a risk of transmitting infectious agents, e. g, viruses, the variant Creutzfeldt-Jakob disease (vCJD) agent, and, theoretically, the Creutzfeldt-Jakob disease (CJD) agent. GAMASTAN is purified from human plasma obtained from healthy donors. When medicinal biological products are administered, infectious diseases due to transmission of pathogens cannot be totally excluded. However, in the case of products prepared from human plasma, the risk of transmission of pathogens is reduced by: (1) epidemiological controls on the donor population and selection of individual donors by a medical interview and screening of individual donations and plasma pools for viral infection markers; (2) testing of plasma for hepatitis C virus (HCV), human immunodeficiency virus (HIV), hepatitis B virus (HBV), HAV, and human parvovirus (B19V) genomic material; and (3) manufacturing procedures with demonstrated capacity to inactivate/remove pathogens.

No cases of transmission of viral diseases, vCJD, or CJD have ever been identified for products manufactured with the same core manufacturing process as GAMASTAN. ALL infections suspected by a physician possibly to have been transmitted by this product should be reported by the physician or other healthcare provider to Grifols Therapeutics LLC [1-800-520-2807].

6 ADVERSE REACTIONS

The most common adverse reaction reported for GAMASTAN S/D during post-approval use was fatigue.

6.2 Postmarketing Experience

The following adverse reactions have been identified during post-approval use with GAMASTAN made using the previous manufacturing process, GAMASTAN S/D. Because these reactions are reported voluntarily from a population of uncertain size, it is not always possible to reliably estimate their frequency or establish a causal relationship to drug exposure.

Among patients treated with GAMASTAN S/D, cases of allergic/hypersensitivity reactions including anaphylaxis have been reported. Anaphylactic reactions, although rare, have been reported following the injection of human immune globulin preparations.(11) Anaphylaxis was more likely to occur if GAMASTAN S/D was given intravenously; therefore, GAMASTAN S/D and GAMASTAN must be administered only intramuscularly.

The following have been identified as the most frequently reported post-marketing adverse reactions.

Immune system disorders | Anaphylactic reaction [These reactions have been manifested by rash, flushing, and dyspnea] , hypersensitivity
Nervous system disorders | Headache
Gastrointestinal disorders | Nausea
General disorders and administration site conditions | Injection site pain, injection site inflammation, fatigue, pyrexia

7 DRUG INTERACTIONS

Antibodies in GAMASTAN may interfere with the response to live virus vaccines such as measles, mumps, polio, rubella, and varicella. Defer live vaccine administration for up to 6 months after GAMASTAN administration.

8 USE IN SPECIFIC POPULATIONS

8.1 Pregnancy

Risk Summary

There are no data with GAMASTAN use in pregnant women to inform a drug-associated risk. Animal reproduction studies have not been conducted with GAMASTAN. It is not known whether GAMASTAN can cause fetal harm when administered to a pregnant woman or can affect reproduction capacity. In the U.S. general population, the estimated background risk of major birth defect and miscarriage in clinically recognized pregnancies is 2% to 4% and 15% to 20%, respectively.

8.2 Lactation

Risk Summary

There is no information regarding the presence of GAMASTAN in human milk, the effect on the breastfed infant, or the effects on milk production. The developmental and health benefits of breastfeeding should be considered along with the mother’s clinical need for GAMASTAN and any potential adverse effects on the breastfed infant from GAMASTAN or from the underlying maternal condition.

8.4 Pediatric Use

Safety and effectiveness in the pediatric population have not been established.

8.5 Geriatric Use

Safety and effectiveness in the geriatric population have not been established.

11 DESCRIPTION

GAMASTAN is a clear or slightly opalescent, and colorless or pale yellow sterile solution of polyvalent human immune globulin for intramuscular administration. GAMASTAN contains no preservative. GAMASTAN is prepared from pools of human plasma collected from healthy donors by a combination of cold ethanol fractionation, caprylate precipitation and filtration, caprylate incubation, anion-exchange chromatography, nanofiltration and low pH incubation. GAMASTAN consists of 15% to18% protein at pH of 4.1 to 4.8 in 0.16 to 0.26 M glycine.

When medicinal biological products are administered, infectious diseases due to transmission of pathogens cannot be totally excluded. However, in the case of products prepared from human plasma, the risk of transmission of pathogens is reduced by epidemiological surveillance of the donor population and selection of individual donors by medical interview; testing of individual donations and plasma pools; and the presence in the manufacturing processes of steps with demonstrated capacity to inactivate/remove pathogens.

In the manufacturing process of GAMASTAN, there are several steps with the capacity for viral inactivation or removal. The main steps of the manufacturing process that contribute to the virus clearance capacity are as follows:

- Caprylate precipitation/depth filtration
- Caprylate incubation
- Depth filtration
- Column chromatography
- Nanofiltration
- Low pH final container incubation

To provide additional assurance of the pathogen safety of the final product, the capacity of the GAMASTAN manufacturing process to remove and/or inactivate viruses has been demonstrated by laboratory spiking studies on a scaled down process model using a wide range of viruses with diverse physicochemical properties.

The combination of all of the above mentioned measures provides the final product with a high margin of safety from the potential risk of transmission of infectious viruses.

The caprylate/chromatography manufacturing process was also investigated for its capacity to decrease the infectivity of an experimental agent of transmissible spongiform encephalopathy (TSE), considered as a model for the variant Creutzfeldt-Jakob disease (vCJD), and Creutzfeldt-Jakob disease (CJD) agents.(15) These studies provide reasonable assurance that low levels of vCJD/CJD agent infectivity, if present in the starting material, would be removed by the caprylate/chromatography manufacturing process.

12 CLINICAL PHARMACOLOGY

12.1 Mechanism of Action

The polyclonal antibody in GAMASTAN is a passive immunizing agent to neutralize viruses, such as hepatitis A and measles viruses, to prevent or ameliorate disease.

12.2 Pharmacodynamics

The prophylactic value of GAMASTAN is greatest when given before or soon after exposure.

12.3 Pharmacokinetics

Peak levels of immunoglobulin G are obtained approximately two days after intramuscular injection of GAMASTAN.(16) The half-life of IgG in the circulation of individuals with normal IgG levels is 23 days.(17)

In a clinical study, 12 healthy human subjects received a 20 IU/kg intramuscular dose of HYPERRAB [rabies immune globulin (human)] made using the same manufacturing process as GAMASTAN. Detectable passive rabies neutralizing antibody was present by 24 hours and persisted through the 21 day follow-up evaluation period. The figure below shows the mean levels of rabies virus antibodies in IU/mL across the 21 day evaluation period and indicates that the titer remains stable during this period.

15 REFERENCES

1. Centers for Disease Control and Prevention. Prevention of hepatitis A through active or passive immunization. Recommendations of the Advisory Committee on Immunization Practices (ACIP). MMWR. 2006;55(RR-07):1-23.
2. Centers for Disease Control and Prevention. Update: Prevention of hepatitis A after exposure to hepatitis A virus and in international travelers. Updated recommendations of the Advisory Committee on Immunization Practices (ACIP). MMWR. 2007;56(41);1080-4.
3. Centers for Disease Control and Prevention. Measles, mumps, and rubella - Vaccine use and strategies for elimination of measles, rubella, and congenital rubella syndrome and control of mumps: Recommendations of the Advisory Committee on Immunization Practices (ACIP). MMWR. 1998;47(RR-08):1-57.
4. Centers for Disease Control and Prevention. General recommendations on immunization. Recommendations of the Advisory Committee on Immunization Practices (ACIP). MMWR. 2011;60(RR02):1-61.
5. Centers for Disease Control and Prevention. Prevention of varicella. Recommendations of the Advisory Committee on Immunization Practices (ACIP). MMWR. 2007;56(RR04):1-40.
6. Gershon AA, Piomelli S, Karpatkin M, et al. Antibody to varicella-zoster virus after passive immunization against chickenpox. J Clin Microbiol. 1978;8(6): 733-5.
7. Centers for Disease Control and Prevention. Prevention of measles, rubella, congenital rubella syndrome, and mumps: Summary recommendations of the Advisory Committee on Immunization Practices (ACIP). MMWR. 2013;62(RR-04):17-8.
8. Centers for Disease Control and Prevention. A comprehensive immunization strategy to eliminate transmission of hepatitis B virus infection in the United States. Recommendations of the Advisory Committee on Immunization Practices (ACIP). Part II. Immunization of adults. MMWR. 2006;55(RR-16):1-33.
9. Zaaijer HL, Leentvaar-Kuijpers A, Rotman H, et al. Hepatitis A antibody titres after infection and immunization: implications for passive and active immunization. J Med Virol. 1993;40:22-7.
10. Tejada-Strop A, Costafreda MI, Dimitrova Z, et al. Evaluation of potencies of immune globulin products against hepatitis A. JAMA Intern. Med. 2017;177(3):430-2.
11. Fudenberg HH. Sensitization to immunoglobulins and hazards of gamma globulin therapy. In: Merler E, editor. Immunoglobulins: biologic aspects and clinical uses. Washington DC: National Academy of Sciences; 1970, p. 211-20.
12. Dalakas MC. High-dose intravenous immunoglobulin and serum viscosity: risk of precipitating thromboembolic events. Neurology. 1994;44:223-6.
13. Woodruff RK, Grigg AP, Firkin FC, et al. Fatal thrombotic events during treatment of autoimmune thrombocytopenia with intravenous immunoglobulin in elderly patients. Lancet. 1986;2:217-8.
14. Wolberg AS, Kon RH, Monroe DM, et al. Coagulation factor XI is a contaminant in intravenous immunoglobulin preparations. Am J Hematol. 2000;65,30-4.
15. Barnette D, Roth NJ, Hotta J, et al. Pathogen safety profile of a 10% IgG preparation manufactured using a depth filtration-modified process. Biologicals. 2012;40:247-53.
16. Smith GN, Griffiths B, Mollison D, et al. Uptake of IgG after intramuscular and subcutaneous injection. Lancet. 1972;1(7762): 1208-12.
17. Waldmann TA, Strober W, Blaese RM. Variations in the metabolism of immunoglobulins measured by turnover rates. In: Merler E, editor. Immunoglobulins: biologic aspects and clinical uses. Washington, DC: National Academy of Sciences; 1970, p. 33-51.

16 HOW SUPPLIED/STORAGE AND HANDLING

GAMASTAN is supplied in 2 mL and 10 mL single dose vials. GAMASTAN contains no preservative and is not made with natural rubber latex.

NDC Number | Size
13533-335-04 | 2 mL vial
13533-335-12 | 10 mL vial

- Store GAMASTAN at 2°C to 8°C (36°F to 46°F).
- Do not freeze.
- Do not use after expiration date.

17 PATIENT COUNSELING INFORMATION

- Discuss the risks and benefits of this product with the patient, before prescribing or administering it to the patient.
- Instruct the patient to immediately report symptoms of thrombosis. These symptoms may include: pain and/or swelling of an arm or leg with warmth over the affected area, discoloration of an arm or leg, unexplained shortness of breath, chest pain or discomfort that worsens on deep breathing, unexplained rapid pulse, numbness or weakness on one side of the body. [see Warnings and Precautions (5.2)]
- Inform the patient that GAMASTAN is made from human plasma and may carry a risk of transmitting infectious agents that can cause disease. While the risk that GAMASTAN can transmit an infectious agent has been reduced by screening plasma donors for prior exposure, testing donated plasma, and including manufacturing steps with the capacity to inactivate and/ or remove pathogens, instruct the patient to report any symptoms that concern them. [see Boxed Warning, Warnings and Precautions (5.4)]
- Inform the patient that GAMASTAN can interfere with their immune response to live virus vaccines such as measles, mumps and rubella. Inform patients to notify their healthcare professional of this potential interaction when they are receiving vaccinations. [see Drug Interactions (7)]

Manufactured by:

Grifols Therapeutics LLC

Research Triangle Park, NC 27709 USA

U.S. License No. 1871

3063873

PRINCIPAL DISPLAY PANEL

LEFT PANEL
NDC 13533-335-12 10 mL
Immune
Globulin
(Human)
GamaSTAN®
10 mL
Solution for
Intramuscular Injection
Rx only
FOR INTRAMUSCULAR
INJECTION ONLY.
DO NOT GIVE INTRAVENOUSLY.
GRIFOLS
TOP FLAP
NDC 13533-335-12
GTIN 00313533335120
LOT XXXXXXXXXX
EXP DDMMMYY
SN XXXXXXXXXXXXXXXX
GamaSTAN® 10 mL
SECOND PANEL
Immune Globulin (Human) is a
sterile solution of immuno-
globulin containing 15%-18%
protein stabilized with 0.16 to
0.26 M glycine.
No U.S. standard of potency for
viral hepatitis antibodies.
10 mL
Not made with natural rubber
latex.
No preservative
Grifols Therapeutics LLC
Research Triangle Park,
NC 27709 USA
U.S. License No. 1871
GRIFOLS
THIRD PANEL
NDC 13533-335-12 10 mL
Immune
Globulin
(Human)
GamaSTAN®
10 mL
Solution for
Intramuscular Injection
Rx only
FOR INTRAMUSCULAR
INJECTION ONLY.
DO NOT GIVE INTRAVENOUSLY.
GRIFOLS
Bottom Tab
Carton: 3060459
RIGHT PANEL
The patient and physician
should discuss the risks and
benefits of this product.
One Single-dose Vial
For complete dosage and
administration information,
read enclosed package insert.
Store at 2-8°C (36-46°F).
Do not freeze.
10 mL
Discard unused portion.
If the shrink band is absent or
shows any sign of tampering,
do not use the product and
notify Grifols Therapeutics LLC
immediately.
Not returnable for credit or
exchange.
GRIFOLS

NDC 13533-335-13 10 mL
Immune Globulin (Human)
GamaSTAN®
The patient and physician should discuss
the risks and benefits of this product.
One Single-dose Vial
Do not give intravenously.
Dosage: Read package insert.
Grifols Therapeutics LLC
RTP, NC 27709 USA
Rx only
U.S. License No. 1871
3060451
Lot/Exp.